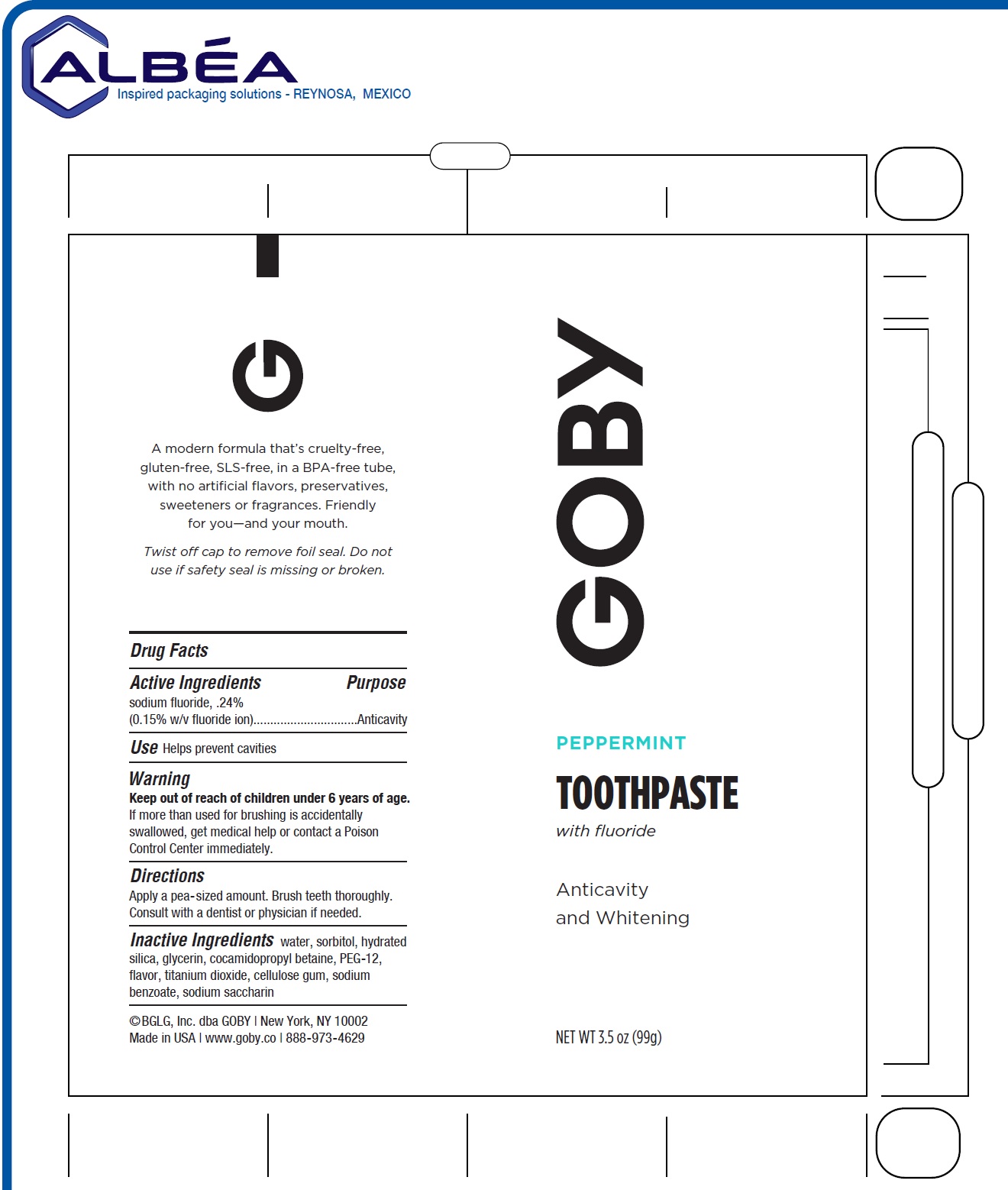 DRUG LABEL: Goby Peppermint
NDC: 81788-001 | Form: PASTE
Manufacturer: BGLG, Inc.
Category: otc | Type: HUMAN OTC DRUG LABEL
Date: 20210419

ACTIVE INGREDIENTS: SODIUM FLUORIDE 2.4 mg/1 g
INACTIVE INGREDIENTS: WATER; SORBITOL; HYDRATED SILICA; GLYCERIN; COCAMIDOPROPYL BETAINE; POLYETHYLENE GLYCOL 600; METHYL SALICYLATE; TITANIUM DIOXIDE; CARBOXYMETHYLCELLULOSE SODIUM, UNSPECIFIED; SODIUM BENZOATE; SACCHARIN SODIUM

Goby peppermint Toothpaste

Active Ingredients

sodium fluoride, .24%
(0.15% w/v fluoride ion)

Purpose

Anticavity

Use

Helps prevent cavities

Warning

Keep out of reach of children

under 6 years of age.
If more than used for brushing is accidentally swallowed, get medical help or contact a Poison Control Center immediately.

Directions

Apply a pea-sized amount. Brush teeth thoroughly. Consult with a dentist or physician if needed.

Inactive Ingredients

water, sorbitol, hydrated silica, glycerin, cocamidopropyl betaine, PEG-12, flavor, titanium dioxide, cellulose gum, sodium benzoate, sodium saccharin